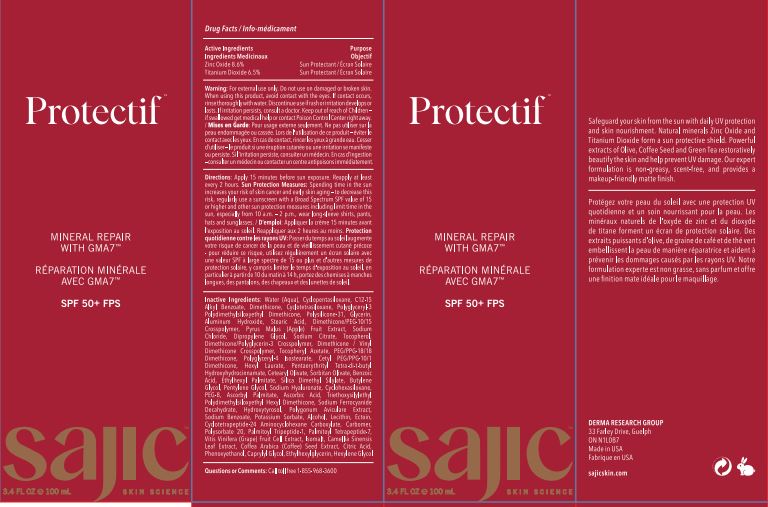 DRUG LABEL: Protectif untinted
NDC: 82038-004 | Form: CREAM
Manufacturer: Derma Research Group Inc.
Category: otc | Type: HUMAN OTC DRUG LABEL
Date: 20220627

ACTIVE INGREDIENTS: TITANIUM DIOXIDE 6.5 g/100 g; ZINC OXIDE 8.6 g/100 g
INACTIVE INGREDIENTS: PEG/PPG-18/18 DIMETHICONE; SILICA DIMETHYL SILYLATE; PENTYLENE GLYCOL; ALCOHOL; ALUMINUM HYDROXIDE; DIMETHICONE/PEG-10/15 CROSSPOLYMER; SODIUM CITRATE; WATER; PENTAERYTHRITOL TETRAKIS(3-(3,5-DI-TERT-BUTYL-4-HYDROXYPHENYL)PROPIONATE); SORBITAN OLIVATE; ASCORBYL PALMITATE; APPLE; SODIUM CHLORIDE; HEXYL LAURATE; CETEARYL OLIVATE; ASCORBIC ACID; SODIUM FERROCYANIDE DECAHYDRATE; SODIUM BENZOATE; HYDROXYTYROSOL; BUTYLENE GLYCOL; HYALURONATE SODIUM; CETYL PEG/PPG-10/1 DIMETHICONE (HLB 4); CYCLOMETHICONE 6; POLYGONUM AVICULARE TOP; CARBOMER HOMOPOLYMER, UNSPECIFIED TYPE; POLYSORBATE 20; PALMITOYL TETRAPEPTIDE-7; CITRIC ACID MONOHYDRATE; ISOMALT; GREEN TEA LEAF; CYCLOMETHICONE 5; ALKYL (C12-15) BENZOATE; ARABICA COFFEE BEAN; CAPRYLYL GLYCOL; ETHYLHEXYLGLYCERIN; .ALPHA.-TOCOPHEROL ACETATE; POLYGLYCERYL-3 POLYDIMETHYLSILOXYETHYL DIMETHICONE (4000 MPA.S); DIPROPYLENE GLYCOL; DIMETHICONE/POLYGLYCERIN-3 CROSSPOLYMER; HEXYLENE GLYCOL; BENZOIC ACID; ETHYLHEXYL PALMITATE; DIMETHICONE/VINYL DIMETHICONE CROSSPOLYMER (SOFT PARTICLE); STEARIC ACID; TOCOPHEROL; POLYETHYLENE GLYCOL 400; TRIETHOXYSILYLETHYL POLYDIMETHYLSILOXYETHYL HEXYL DIMETHICONE; VINYL DIMETHICONE/METHICONE SILSESQUIOXANE CROSSPOLYMER; CYCLOMETHICONE 4; CYCLOTETRAPEPTIDE-24 AMINOCYCLOHEXANE CARBOXYLATE; VITIS VINIFERA STEM; ECTOINE; PHENOXYETHANOL; DIMETHICONE; GLYCERIN; POTASSIUM SORBATE; LECITHIN, SOYBEAN; PALMITOYL TRIPEPTIDE-1; POLYGLYCERYL-4 ISOSTEARATE

Drug Facts

Active Ingredients

Zinc Oxide 8.6 %

Titanium Dioxide 6.5 %

Purpose

Sun Protectant

Uses

Helps Prevent sunburn

Warning

For external use only.

Do not use

Do not use on damaged or broken skin

When using

When using this product, avoid contect with eyes.If contect occurs, rinse throughly with water.

stop use

Discontinue use if rash or irritation develops or lasts. If irritation persists,consultant a doctor

Keep out of reach of children

If swallowed get medical help or contect poison control center right away

DOSAGE AND ADMINISTRATION

Directions: Apply 15 minutes before sun exposure. Reapply at least every 2 hours. Sun Protection Measures: Spending time in the sun increases your risk of skin cancer and early skin aging - to decrease this risk, regularly use a sunscreen with a Broad Spectrum SPF value of 15 or higher and other sun protection measures including limit time in the sun, especially from 10 a.m. - 2 p.m., wear long-sleeve shirts, pants, hats and sunglasses.

OTHER SAFETY INFORMATION

NA

Inactive Ingredients:

Water (Aqua), Cyclopentasiloxane,C12-15 Alkyl Benzoate,Dimethicone,Cyclotetrasiloxane, Polyglyceryl-3 Polydimethylsiloxyethyl Dimethicone, Polysilicone-31,Glycerin, Aluminum Hydroxide,Stearic Acid,Dimethicone/PEG-10/15 Crosspolymer,

Pyrus Malus (Apple) Fruit Extract,Sodium Chloride,Dipropylene Glycol,Sodium Citrate,Tocopherol, DimethiconelPolyglycerin-3 Crosspolymer, Dimethicone /Vinyl Dimethicone Crosspolymer,Tocopheryl Acetate, PEG/PPG-18/18 Dimethicone,

Polyglyceryl-4 Isostearate, Cetyl PEG/PPG-10/1 Dimethicone,Hexyl Laurate,Pentaerythrityl Tetra-di-t-butyl Hydroxyhydrocinnamate, Cetearyl Olivate,Sornitan Olivate, Benzoic Acid, Ethylhexyl Palmitate,Silica Dimethyl Silylate,

Butylene Glycol,Pentylene Glycol,Sodium Hyaluronate,Cyclohexasiloxane, PEG-8,Ascorbyl Palmitate,Ascorbic Acid,

Triethoxysilylethyl Polydimethylsiloxyethyl Hexyl Dimethicone, Sodium Ferrocyanide Decahydrate,

Hydroxytyrosol,Polygonum Aviculare Extract,Sodium Benzoate,Potassium Sorbate, Alcohol,Lecithin,Ectoin,

Cyclotetrapeptide-24 Aminocyclohexane Carboxylate, Carbomer,Polysorbate 20, Palmitoyl Tripeptide-1,

Palmitoyl Tetrapeptide-7,VitisVinifera(Grape)Fruit Cell Extract,Isomalt,Camellia Sinensis Leaf Extract,

Coffea Arabica (Coffee) Seed Extract,Citric Acid, Phenoxyethanol,Caprylyl Glycol,Ethylhexylglycerin,Hexylene Glycol